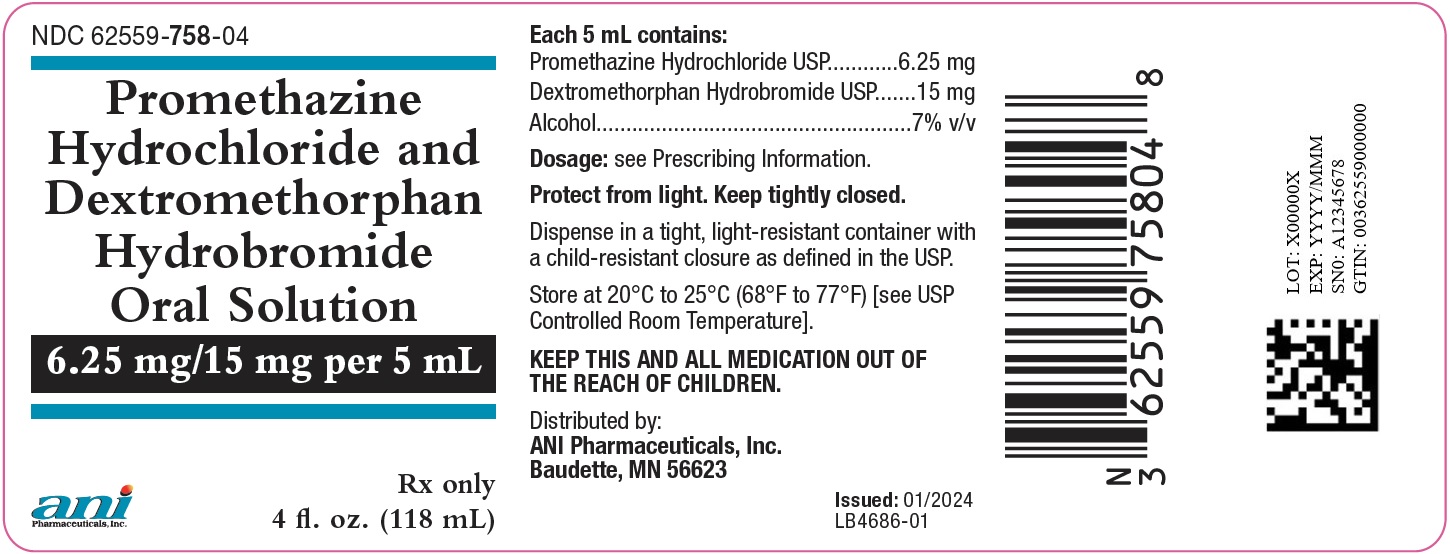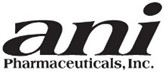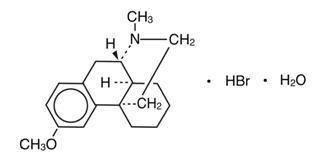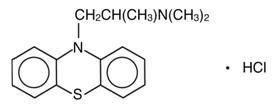 DRUG LABEL: Promethazine Hydrochloride and Dextromethorphan Hydrobromide
NDC: 62559-758 | Form: SOLUTION
Manufacturer: ANI Pharmaceuticals, Inc.
Category: prescription | Type: HUMAN PRESCRIPTION DRUG LABEL
Date: 20250808

ACTIVE INGREDIENTS: PROMETHAZINE HYDROCHLORIDE 6.25 mg/5 mL; DEXTROMETHORPHAN HYDROBROMIDE 15 mg/5 mL
INACTIVE INGREDIENTS: ALCOHOL; ASCORBIC ACID; ANHYDROUS CITRIC ACID; D&C YELLOW NO. 10; EDETATE DISODIUM; FD&C YELLOW NO. 6; GLYCERIN; LEVOMENTHOL; SODIUM BENZOATE; TRISODIUM CITRATE DIHYDRATE; SODIUM PROPIONATE; SACCHARIN SODIUM; SUCROSE; WATER

Promethazine Hydrochloride and Dextromethorphan Hydrobromide Oral Solution
Rx Only

DESCRIPTION

Each 5 mL (teaspoon) of Promethazine Hydrochloride and Dextromethorphan Hydrobromide Oral Solution contains 6.25 mg promethazine hydrochloride USP and 15 mg dextromethorphan hydrobromide USP in a flavored syrup base with a pH between 4.5 and 5.5. The inactive ingredients present are alcohol 7% (v/v), ascorbic acid, citric acid, black currant flavor, D&C Yellow 10, edetate disodium, FD&C Yellow 6, glycerin, L-Menthol, sodium benzoate, sodium citrate, sodium propionate, saccharin sodium, sucrose, and water.

Promethazine hydrochloride USP is a racemic compound; the empirical formula is C17H20N2S•HCl and its molecular weight is 320.88.

Promethazine hydrochloride USP, a phenothiazine derivative, is chemically designated as 10H-Phenothiazine-10-ethanamine, N,N, α-trimethyl-, monohydrochloride, (+)- with the following structural formula:

Promethazine hydrochloride USP occurs as a white to faint yellow, practically odorless, crystalline powder which slowly oxidizes and turns blue on prolonged exposure to air. It is freely soluble in water and soluble in alcohol.

Dextromethorphan hydrobromide USP is a salt of the methyl ether of the dextrorotatory isomer of levorphanol, a narcotic analgesic. It is chemically designated as 3-methoxy-17-methyl-9α, 13α, 14α–morphinan hydrobromide monohydrate with the following structural formula:

Dextromethorphan hydrobromide monohydrate occurs as white crystals, is sparingly soluble in water, and is freely soluble in alcohol. The empirical formula is C18H25NO•HBr•H2O, and the molecular weight of the monohydrate is 370.33. Dextromethorphan hydrobromide monohydrate is dextrorotatory with a specific rotation of +27.6 degrees in water (20 degrees C, sodium D-line).

CLINICAL PHARMACOLOGY

PROMETHAZINE

Promethazine is a phenothiazine derivative which differs structurally from the antipsychotic phenothiazines by the presence of a branched side chain and no ring substitution. It is thought that this configuration is responsible for its relative lack (1/10 that of chlorpromazine) of dopamine antagonist properties.

Promethazine is an H1 receptor blocking agent. In addition to its antihistaminic action, it provides clinically useful sedative and antiemetic effects.

Promethazine is well absorbed from the gastrointestinal tract. Clinical effects are apparent within 20 minutes after oral administration and generally last four to six hours, although they may persist as long as 12 hours.

Promethazine is metabolized by the liver to a variety of compounds; the sulfoxides of promethazine and N-demethylpromethazine are the predominant metabolites appearing in the urine.

DEXTROMETHORPHAN

Dextromethorphan is an antitussive agent and, unlike the isomeric levorphanol, it has no analgesic or addictive properties.

Dextromethorphan acts centrally and elevates the threshold for coughing. It is about equal to codeine in depressing the cough reflex. In therapeutic dosage dextromethorphan does not inhibit ciliary activity.

Dextromethorphan is rapidly absorbed from the gastrointestinal tract and exerts its effect in 15 to 30 minutes. The duration of action after oral administration is approximately three to six hours.

Dextromethorphan is metabolized primarily by liver enzymes undergoing O-demethylation, N-demethylation, and partial conjugation with glucuronic acid and sulfate. In humans, (+)-3-hydroxy-N-methylmorphinan, (+)-3-hydroxymorphinan, and traces of unmetabolized drug were found in urine after oral administration.

INDICATIONS AND USAGE

Promethazine Hydrochloride and Dextromethorphan Hydrobromide Oral Solution is indicated for the temporary relief of coughs and upper respiratory symptoms associated with allergy or the common cold.

CONTRAINDICATIONS

Promethazine Hydrochloride and Dextromethorphan Hydrobromide Oral Solution is contraindicated for use in pediatric patients less than two years of age.

Promethazine is contraindicated in comatose states, and in individuals known to be hypersensitive or to have had an idiosyncratic reaction to promethazine or to other phenothiazines.

Antihistamines are contraindicated for use in the treatment of lower respiratory tract symptoms, including asthma.

Dextromethorphan should not be used in patients receiving a monoamine oxidase inhibitor (see PRECAUTIONS – Drug Interactions).

WARNINGS

BOXED WARNING

Promethazine Hydrochloride and Dextromethorphan Hydrobromide Oral Solution should not be used in pediatric patients less than 2 years of age because of the potential for fatal respiratory depression.

Postmarketing cases of respiratory depression, including fatalities, have been reported with use of promethazine in pediatric patients less than 2 years of age. A wide range of weight-based doses of promethazine have resulted in respiratory depression in these patients.

Caution should be exercised when administering promethazine to pediatric patients 2 years of age and older. It is recommended that the lowest effective dose of promethazine be used in pediatric patients 2 years of age and older and concomitant administration of other drugs with respiratory depressant effects be avoided.

PROMETHAZINE

CNS Depression

Promethazine may impair the mental and/or physical abilities required for the performance of potentially hazardous tasks, such as driving a vehicle or operating machinery. The impairment may be amplified by concomitant use of other central-nervous-system depressants such as alcohol, sedatives/hypnotics (including barbiturates), narcotics, narcotic analgesics, general anesthetics, tricyclic antidepressants, and tranquilizers; therefore such agents should either be eliminated or given in reduced dosage in the presence of promethazine (see PRECAUTIONS – Information for Patients and Drug Interactions).

Respiratory Depression

Promethazine may lead to potentially fatal respiratory depression.

Use of Promethazine Hydrochloride and Dextromethorphan Hydrobromide Oral Solution in patients with compromised respiratory function (e.g. COPD, sleep apnea syndrome) should be avoided.

Lower Seizure Threshold

Promethazine may lower seizure threshold. It should be used with caution in persons with seizure disorders or in persons who are using concomitant medications, such as narcotics or local anesthetics, which may also affect seizure threshold.

Bone-Marrow Depression

Promethazine Hydrochloride and Dextromethorphan Hydrobromide Oral Solution should be used with caution in patients with bone-marrow depression. Leukopenia and agranulocytosis have been reported, usually when promethazine has been used in association with other known marrow-toxic agents.

Neuroleptic Malignant Syndrome

A potentially fatal symptom complex sometimes referred to as Neuroleptic Malignant Syndrome (NMS) has been reported in association with promethazine alone or in combination with antipsychotic drugs. Clinical manifestations of NMS are hyperpyrexia, muscle rigidity, altered mental status and evidence of autonomic instability (irregular pulse or blood pressure, tachycardia, diaphoresis and cardiac dysrhythmias).

The diagnostic evaluation of patients with this syndrome is complicated. In arriving at a diagnosis, it is important to identify cases where the clinical presentation includes both serious medical illness (e.g. pneumonia, systemic infection, etc.) and untreated or inadequately treated extrapyramidal signs and symptoms (EPS). Other important considerations in the differential diagnosis include central anticholinergic toxicity, heat stroke, drug fever and primary central nervous system (CNS) pathology.

The management of NMS should include 1) immediate discontinuation of promethazine, antipsychotic drugs, if any, and other drugs not essential to concurrent therapy, 2) intensive symptomatic treatment and medical monitoring, and 3) treatment of any concomitant serious medical problems for which specific treatments are available. There is no general agreement about specific pharmacological treatment regimens for uncomplicated NMS.

Since recurrences of NMS have been reported with phenothiazines, the reintroduction of promethazine should be carefully considered.

Use in Pediatric Patients

Promethazine Hydrochloride and Dextromethorphan Hydrobromide Oral Solution is contraindicated for use in pediatric patients less than two years of age.

Caution should be exercised when administering Promethazine Hydrochloride and Dextromethorphan Hydrobromide Oral Solution to pediatric patients 2 years of age and older because of the potential for fatal respiratory depression. Respiratory depression and apnea, sometimes associated with death, are strongly associated with promethazine products and are not directly related to individualized weight-based dosing, which might otherwise permit safe administration. Concomitant administration of promethazine products with other respiratory depressants has an association with respiratory depression, and sometimes death, in pediatric patients.

Antiemetics are not recommended for treatment of uncomplicated vomiting in pediatric patients, and their use should be limited to prolonged vomiting of known etiology. The extrapyramidal symptoms which can occur secondary to Promethazine Hydrochloride and Dextromethorphan Hydrobromide Oral Solution administration may be confused with the CNS signs of undiagnosed primary disease, e.g., encephalopathy or Reye’s syndrome. The use of Promethazine Hydrochloride and Dextromethorphan Hydrobromide Oral Solution should be avoided in pediatric patients whose signs and symptoms may suggest Reye’s syndrome or other hepatic diseases.

Excessively large dosages of antihistamines, including promethazine, in pediatric patients may cause sudden death (see OVERDOSAGE). Hallucinations and convulsions have occurred with therapeutic doses and overdoses of Promethazine in pediatric patients.

In pediatric patients who are acutely ill associated with dehydration, there is an increased susceptibility to dystonias with the use of promethazine.

Other Considerations

Administration of promethazine has been associated with reported cholestatic jaundice.

DEXTROMETHORPHAN

Administration of dextromethorphan may be accompanied by histamine release and should be used with caution in atopic children.

PRECAUTIONS

General

Drugs having anticholinergic properties should be used with caution in patients with narrow-angle glaucoma, prostatic hypertrophy, stenosing peptic ulcer, pyloroduodenal obstruction and bladder-neck obstruction. Promethazine Hydrochloride and Dextromethorphan Hydrobromide Oral Solution should be used cautiously in persons with cardiovascular disease or with impairment of liver function.

Dextromethorphan should be used with caution in sedated patients, in the debilitated, and in patients confined to the supine position.

Information for Patients

Patients should be advised to measure Promethazine Hydrochloride and Dextromethorphan Hydrobromide Oral Solution with an accurate measuring device. A household teaspoon is not an accurate measuring device and could lead to overdosage, especially when a half a teaspoon is measured. A pharmacist can recommend an appropriate measuring device and can provide instructions for measuring the correct dose.

Promethazine Hydrochloride and Dextromethorphan Hydrobromide Oral Solution may cause marked drowsiness or impair the mental and/or physical abilities required for the performance of potentially hazardous tasks, such as driving a vehicle or operating machinery. Ambulatory patients should be told to avoid engaging in such activities until it is known that they do not become drowsy or dizzy from promethazine and dextromethorphan therapy. Pediatric patients should be supervised to avoid potential harm in bike riding or in other hazardous activities.

The concomitant use of alcohol or other central-nervous-system depressants, such as sedatives/hypnotics (including barbiturates), narcotics, narcotic analgesics, general anesthetics, tricyclic antidepressants, and tranquilizers, may enhance impairment (see WARNINGS – CNS Depression and PRECAUTIONS – Drug Interactions).

Patients should be advised to report any involuntary muscle movements.

Avoid prolonged exposure to the sun.

Drug Interactions

Monoamine Oxidase (MAO) Inhibitors – Hyperpyrexia, hypotension, and death have been reported coincident with the co-administration of monoamine oxidase (MAO) inhibitors and products containing dextromethorphan. Drug interactions, including an increased incidence of extrapyramidal effects, have been reported when some MAO inhibitors and phenothiazines are used concomitantly. Thus, concomitant administration of Promethazine Hydrochloride and Dextromethorphan Hydrobromide Oral Solution and MAO inhibitors should be avoided (see CONTRAINDICATIONS).

CNS Depressants – Promethazine may increase, prolong, or intensify the sedative action of other central-nervous-system depressants, such as alcohol, sedatives/hypnotics (including barbiturates), narcotics, narcotic analgesics, general anesthetics, tricyclic antidepressants, and tranquilizers; therefore, such agents should be avoided or administered in reduced dosage to patients receiving promethazine. When given concomitantly with Promethazine Hydrochloride and Dextromethorphan Hydrobromide Oral Solution, the dose of barbiturates should be reduced by at least one-half, and the dose of narcotics should be reduced by one-quarter to one-half. Dosage must be individualized. Excessive amounts of promethazine relative to a narcotic may lead to restlessness and motor hyperactivity in the patient with pain; these symptoms usually disappear with adequate control of the pain.

Epinephrine – Because of the potential for promethazine to reverse epinephrine’s vasopressor effect, epinephrine should NOT be used to treat hypotension associated with Promethazine Hydrochloride and Dextromethorphan Hydrobromide Oral Solution overdose.

Anticholinergics – Concomitant use of other agents with anticholinergic properties should be undertaken with caution.

Drug/Laboratory Test Interactions

The following laboratory tests may be affected in patients who are receiving therapy with promethazine:

Pregnancy Tests

Diagnostic pregnancy tests based on immunological reactions between HCG and anti-HCG may result in false-negative or false-positive interpretations.

Glucose Tolerance Test

An increase in blood glucose has been reported in patients receiving promethazine.

Carcinogenesis, Mutagenesis, Impairment of Fertility

Long-term animal studies have not been performed to assess the carcinogenic potential of promethazine or of dextromethorphan. There are no animal or human data concerning carcinogenicity, mutagenicity, or impairment of fertility with these drugs. Promethazine was nonmutagenic in the Salmonella test system of Ames.

Pregnancy

Teratogenic Effects

Teratogenic effects have not been demonstrated in rat-feeding studies at doses of 6.25 and 12.5 mg/kg of promethazine. These doses are 8.3 and 16.7 times the maximum recommended total daily dose for a 50-kg subject. Daily doses of 25 mg/kg intraperitoneally have been found to produce fetal mortality in rats.

Specific studies to test the action of promethazine on parturition, lactation, and development of the animal neonate were not done, but a general preliminary study in rats indicated no effect on these parameters. Although antihistamines, including promethazine, have been found to produce fetal mortality in rodents, the pharmacological effects of histamine in the rodent do not parallel those in man. There are no adequate and well-controlled studies of promethazine in pregnant women.

Animal reproduction studies have not been conducted with the drug combination – promethazine and dextromethorphan. It is not known whether this drug combination can cause fetal harm when administered to a pregnant woman or can affect reproduction capacity. Promethazine Hydrochloride and Dextromethorphan Hydrobromide Oral Solution should be given to a pregnant woman only if clearly needed. Promethazine Hydrochloride and Dextromethorphan Hydrobromide Oral Solution should be used during pregnancy only if the potential benefit justifies the potential risk to the fetus.

Nonteratogenic Effects

Promethazine administered to a pregnant woman within two weeks of delivery may inhibit platelet aggregation in the newborn.

Labor and Delivery

Limited data suggest that use of promethazine during labor and delivery does not have an appreciable effect on the duration of labor or delivery and does not increase the risk of need for intervention in the newborn. The effect on later growth and development of the newborn is unknown. See also Nonteratogenic Effects.

Nursing Mothers

It is not known whether promethazine or dextromethorphan is excreted in human milk. Because many drugs are excreted in human milk and because of the potential for serious adverse reactions in nursing infants from Promethazine Hydrochloride and Dextromethorphan Hydrobromide Oral Solution, a decision should be made whether to discontinue nursing or to discontinue the drug, taking into account the importance of the drug to the mother.

Pediatric Use

Promethazine Hydrochloride and Dextromethorphan Hydrobromide Oral Solution is contraindicated for use in pediatric patients less than two years of age (seeWARNINGS – Boxed Warning and Use in Pediatric Patients).

Promethazine Hydrochloride and Dextromethorphan Hydrobromide Oral Solution should be used with caution in pediatric patients 2 years of age and older (see WARNINGS – Use in Pediatric Patients).

Geriatric Use

Clinical studies of promethazine formulations did not include sufficient numbers of subjects aged 65 and over to determine whether they respond differently from younger subjects. Other reported clinical experience has not identified differences in responses between the elderly and younger patients. In general, dose selection for an elderly patient should be cautious, usually starting at the low end of the dosing range, reflecting the greater frequency of decreased hepatic, renal or cardiac function, and of concomitant disease or other drug therapy.

Sedating drugs may cause confusion and over-sedation in the elderly; elderly patients generally should be started on low doses of Promethazine Hydrochloride and Dextromethorphan Hydrobromide Oral Solution and observed closely.

ADVERSE REACTIONS

PROMETHAZINE

Central Nervous System – Drowsiness is the most prominent CNS effect of this drug. Sedation, somnolence, blurred vision, dizziness; confusion, disorientation and extrapyramidal symptoms such as oculogyric crisis, torticollis, and tongue protrusion; lassitude, tinnitus, incoordination, fatigue, euphoria, nervousness, diplopia, insomnia, tremors, convulsive seizures, excitation, catatonic-like states, hysteria. Hallucinations have also been reported.

Cardiovascular – Increased or decreased blood pressure, tachycardia, bradycardia, faintness.

Dermatologic – Dermatitis, photosensitivity, urticaria.

Hematologic – Leukopenia, thrombocytopenia, thrombocytopenic purpura, agranulocytosis.

Gastrointestinal – Dry mouth, nausea, vomiting, jaundice.

Respiratory – Asthma, nasal stuffiness, respiratory depression (potentially fatal) and apnea (potentially fatal) (see WARNINGS – Respiratory Depression.)

Other – Angioneurotic edema. Neuroleptic malignant syndrome (potentially fatal) has also been reported (see WARNINGS – Neuroleptic Malignant Syndrome.)

Paradoxical Reactions

Hyperexcitability and abnormal movements have been reported in patients following a single administration of Promethazine Hydrochloride and Dextromethorphan Hydrobromide Oral Solution. Consideration should be given to the discontinuation of promethazine Hydrochloride and to the use of other drugs if these reactions occur. Respiratory depression, nightmares, delirium, and agitated behavior have also been reported in some of these patients.

DEXTROMETHORPHAN

Dextromethorphan occasionally causes slight drowsiness, dizziness, and gastrointestinal disturbances.

To report SUSPECTED ADVERSE REACTIONS, contact ANI Pharmaceuticals, Inc. at 1-855-204-1431 or FDA at 1-800-FDA-1088 or www.fda.gov/medwatch.

DRUG ABUSE AND DEPENDENCE

According to the WHO Expert Committee on Drug Dependence, dextromethorphan could produce very slight psychic dependence but no physical dependence.

OVERDOSAGE

PROMETHAZINE

Signs and symptoms of overdosage with promethazine range from mild depression of the central nervous system and cardiovascular system to profound hypotension, respiratory depression, unconsciousness, and sudden death. Other reported reactions include hyperreflexia, hypertonia, ataxia, athetosis and extensor-plantar reflexes (Babinski reflex).

Stimulation may be evident, especially in children and geriatric patients. Convulsions may rarely occur. A paradoxical-type reaction has been reported in children receiving single doses of 75 mg to 125 mg orally, characterized by hyperexcitability and nightmares.

Atropine-like signs and symptoms – dry mouth, fixed, dilated pupils, flushing, as well as gastrointestinal symptoms - may occur.

DEXTROMETHORPHAN

Dextromethorphan may produce central excitement and mental confusion. Very high doses may produce respiratory depression. One case of toxic psychosis (hyperactivity, marked visual and auditory hallucinations) after ingestion of a single dose of 20 tablets (300 mg) of dextromethorphan has been reported.

Treatment

Treatment of overdosage with Promethazine Hydrochloride and Dextromethorphan Hydrobromide Oral Solution is essentially symptomatic and supportive. Only in cases of extreme overdosage or individual sensitivity do vital signs, including respiration, pulse, blood pressure, temperature, and EKG, need to be monitored. Activated charcoal orally or by lavage may be given, or sodium or magnesium sulfate orally as a cathartic. Attention should be given to the reestablishment of adequate respiratory exchange through provision of a patent airway and institution of assisted or controlled ventilation. Diazepam may be used to control convulsions. Acidosis and electrolyte losses should be corrected. The antidotal efficacy of narcotic antagonists to dextromethorphan has not been established; note that any of the depressant effects of promethazine are not reversed by naloxone. Avoid analeptics, which may cause convulsions.

The treatment of choice for resulting hypotension is administration of intravenous fluids, accompanied by repositioning if indicated. In the event that vasopressors are considered for the management of severe hypotension which does not respond to intravenous fluids and repositioning, the administration of norepinephrine or phenylephrine should be considered. EPINEPHRINE SHOULD NOT BE USED, since its use in a patient with partial adrenergic blockade may further lower the blood pressure. Extrapyramidal reactions may be treated with anticholinergic antiparkinson agents, diphenhydramine, or barbiturates. Oxygen may also be administered.

Limited experience with dialysis indicates that it is not helpful.

DOSAGE AND ADMINISTRATION

It is important that Promethazine Hydrochloride and Dextromethorphan Hydrobromide Oral Solution is measured with an accurate measuring device (see PRECAUTIONS – Information for Patients). A household teaspoon is not an accurate measuring device and could lead to overdosage, especially when half a teaspoon is to be measured. It is strongly recommended that an accurate measuring device be used. A pharmacist can provide an appropriate device and can provide instructions for measuring the correct dose.

Promethazine Hydrochloride and Dextromethorphan Hydrobromide Oral Solution is CONTRAINDICATED for children under 2 years of age (see WARNINGS – Boxed Warning and Use in Pediatric Patients).

The average effective dose for adults is 5 mL (one teaspoon) every 4 to 6 hours, not to exceed 30.0 mL in 24 hours. For children 6 years to under 12 years of age, the dose is 2.5 to 5.0 mL (one-half to one teaspoon) every 4 to 6 hours, not to exceed 20.0 mL in 24 hours. For children 2 years to under 6 years of age, the dose is 1.25 to 2.5 mL (one-quarter to one-half teaspoon) every 4 to 6 hours, not to exceed 10.0 mL in 24 hours.

HOW SUPPLIED

Promethazine Hydrochloride and Dextromethorphan Hydrobromide Oral Solution is a clear, yellow solution supplied as follows:

NDC 62559-758-04 – bottle of 4 fl. oz. (118 mL)

NDC 62559-758-16 – bottle of 16 fl. oz. (473 mL)

Keep bottles tightly closed.

Store at 20° to 25°C (68° to 77°F). [See USP Controlled Room Temperature].

Protect from light.

Dispense in tight, light-resistant container (USP/NF) with a child-resistant closure.

Distributed by
ANI Pharmaceuticals, Inc.
Baudette, MN 56623

Issued: 04/2025
LB4688-02

PACKAGE/LABEL PRINCIPAL DISPLAY PANEL

NDC 62559-758-04
Promethazine Hydrochloride and Dextromethorphan Hydrobromide Oral Solution
6.25 mg/15 mg per 5 mL
Rx only
4 fl. oz. (118 mL)